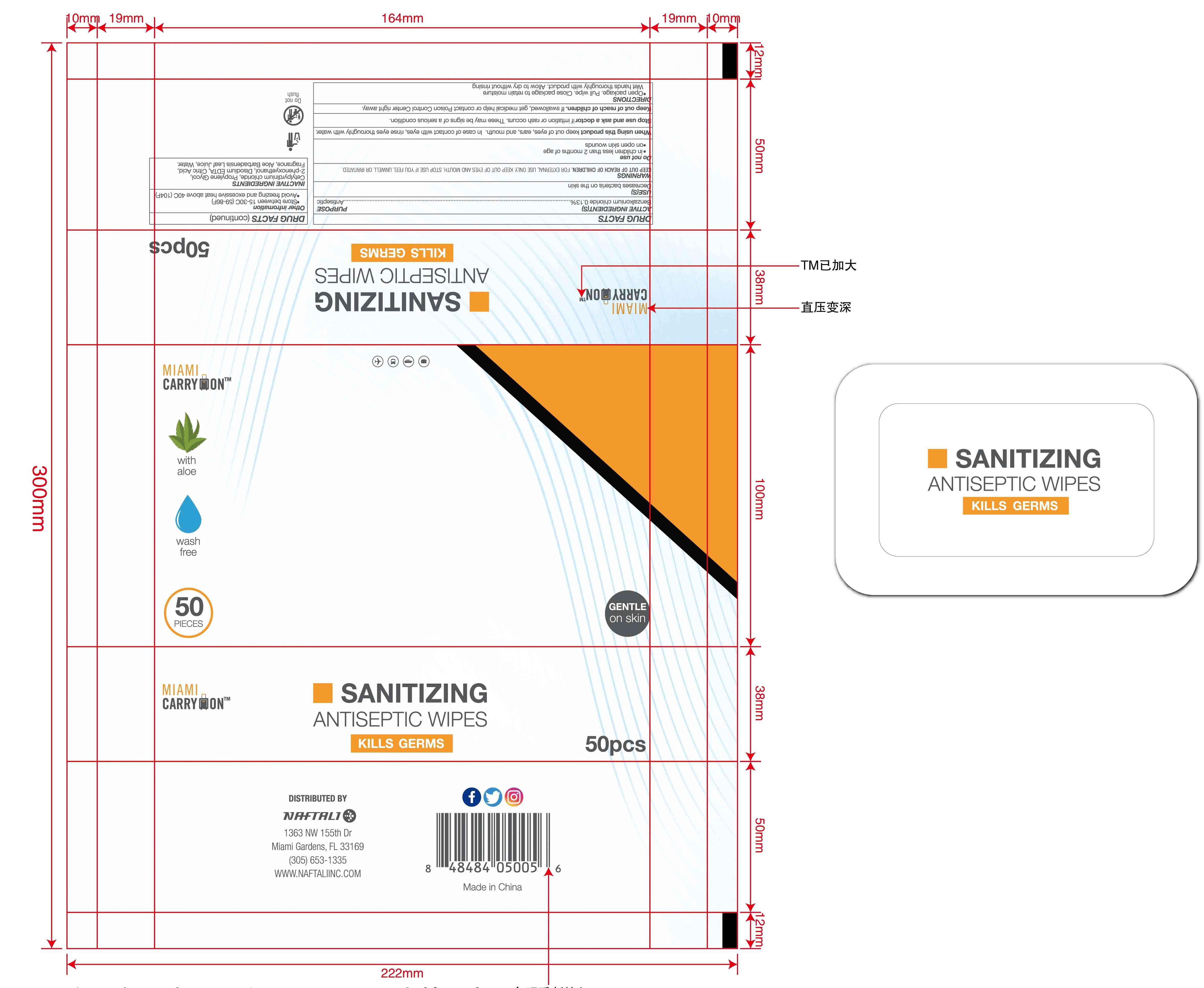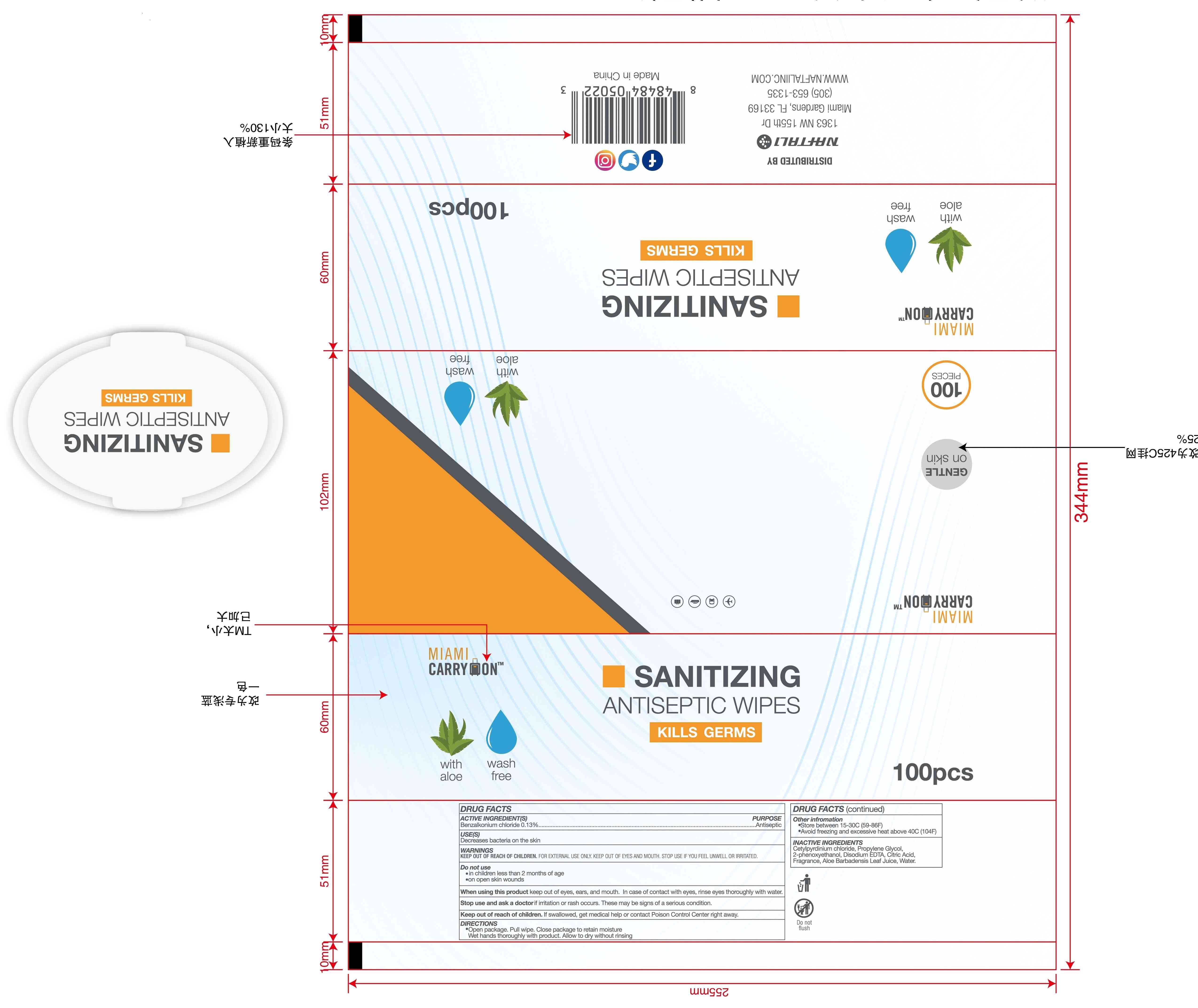 DRUG LABEL: ANTISEPTIC WIPES
NDC: 42003-208 | Form: CLOTH
Manufacturer: Zhejiang Jiayan Daily Commodity Co., Ltd
Category: otc | Type: HUMAN OTC DRUG LABEL
Date: 20220225

ACTIVE INGREDIENTS: BENZALKONIUM CHLORIDE 0.13 g/100 1
INACTIVE INGREDIENTS: PHENOXYETHANOL; EDETATE DISODIUM ANHYDROUS; CITRIC ACID MONOHYDRATE; ALOE VERA LEAF; LEMON; WATER; CETYLPYRIDINIUM CHLORIDE; CHAMOMILE

42003-208
ANTISEPTIC WIPES

Active Ingredient(s)

Benzalkonium chloride 0.13%

Purpose

Antiseptic

Use

Decreases bacteria on the skin

Warnings

KEEP OUT OF REACH OF CHILDREN . FOR EXTERNAL USE ONLY . KEEP OUT OF EYES AND MOUTH . STOP USE IF YOU FEEL UNWELL OR IRRITATED

Do not use

in childr&n less than 2 months of age
on open skin wounds

When using this product keep out of eyes, ears, and mouth. In case of contact with eyes, rinse eyes thoroughly with water.

Stop use and ask a doctor if irritation or rash occurs. These may be signs of a sefious condition.

KEEP OUT OF REACH OF CHILDREN

Keep out of reach o1 children. If swallowed, get medical help or contact Poison Control Center right away.

Directions

Open package. Pull wipe. Close package to retain moisture
Wet hands thoroughly with product.
Allow to dry without rinsing.

Other information

store between 15-30C (59-86F)
Avoid freezing and exessive heat aboce 40C (104F)

Inactive ingredients

Cetylpyrdinium chloride, Propylene Glycol, 2-phenoxyethanol, Disodium EDTA., Citric Acid, Fragrance, Aloe Barbadensis Leaf Juice, Water.